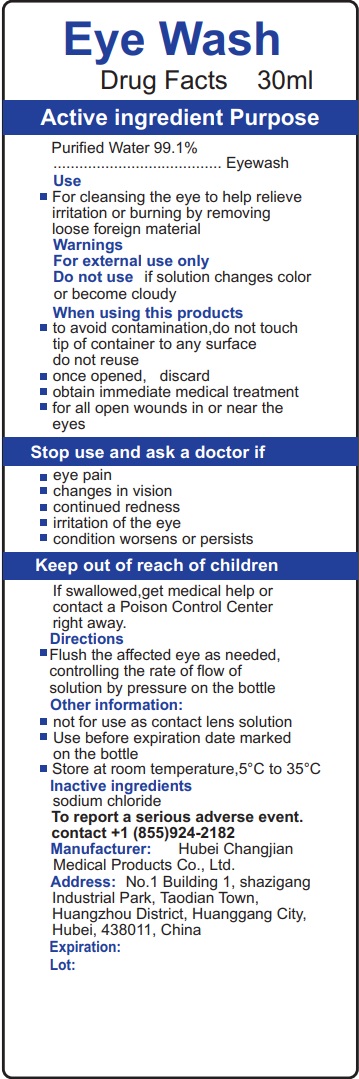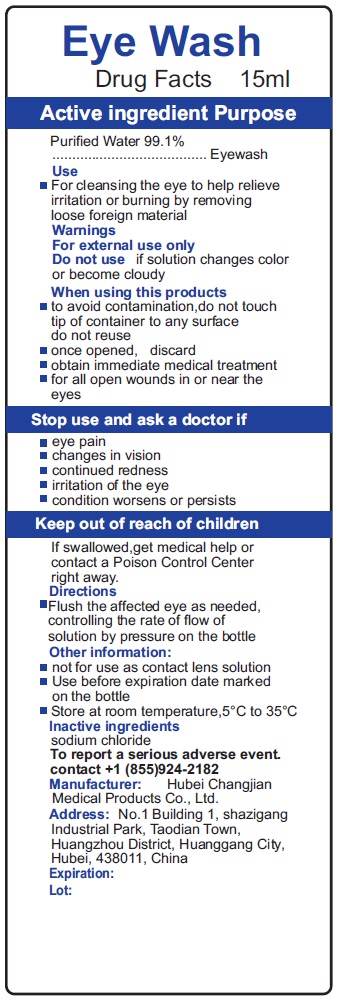 DRUG LABEL: Eye Wash
NDC: 82996-007 | Form: LIQUID
Manufacturer: Hubei Changjian Medical Products Co., Ltd.
Category: otc | Type: HUMAN OTC DRUG LABEL
Date: 20241011

ACTIVE INGREDIENTS: WATER 991 mg/1 mL
INACTIVE INGREDIENTS: SODIUM CHLORIDE

Eye Wash

Active ingredient

Purified Water 99.1%

Purpose

Eyewash

Use

- For cleansing the eye to help relieve irritation or burning by removing loose foreign material

Warnings

For external use only

Do not use

if solution changes color or become cloudy

When using this products

- to avoid contamination,do not touch tip of container to any surface do not reuse
- once opened, discard
- obtain immediate medical treatment
- for all open wounds in or near the eyes

Stop use and ask a doctor if

- eye pain
- changes in vision
- continued redness
- irritation of the eye
- condition worsens or persists

Keep out of reach of children

If swallowed,get medical help or contact a Poison Control Center right away.

Directions

- Flush the affected eye as needed, controlling the rate of flow of solution by pressure on the bottle

Other information:

- not for use as contact lens solution
- Use before expiration date marked on the bottle
- Store at room temperature,5°C to 35°C

lnactive ingredients

sodium chloride

To report a serious adverse event. contact +1 (855)924-2182